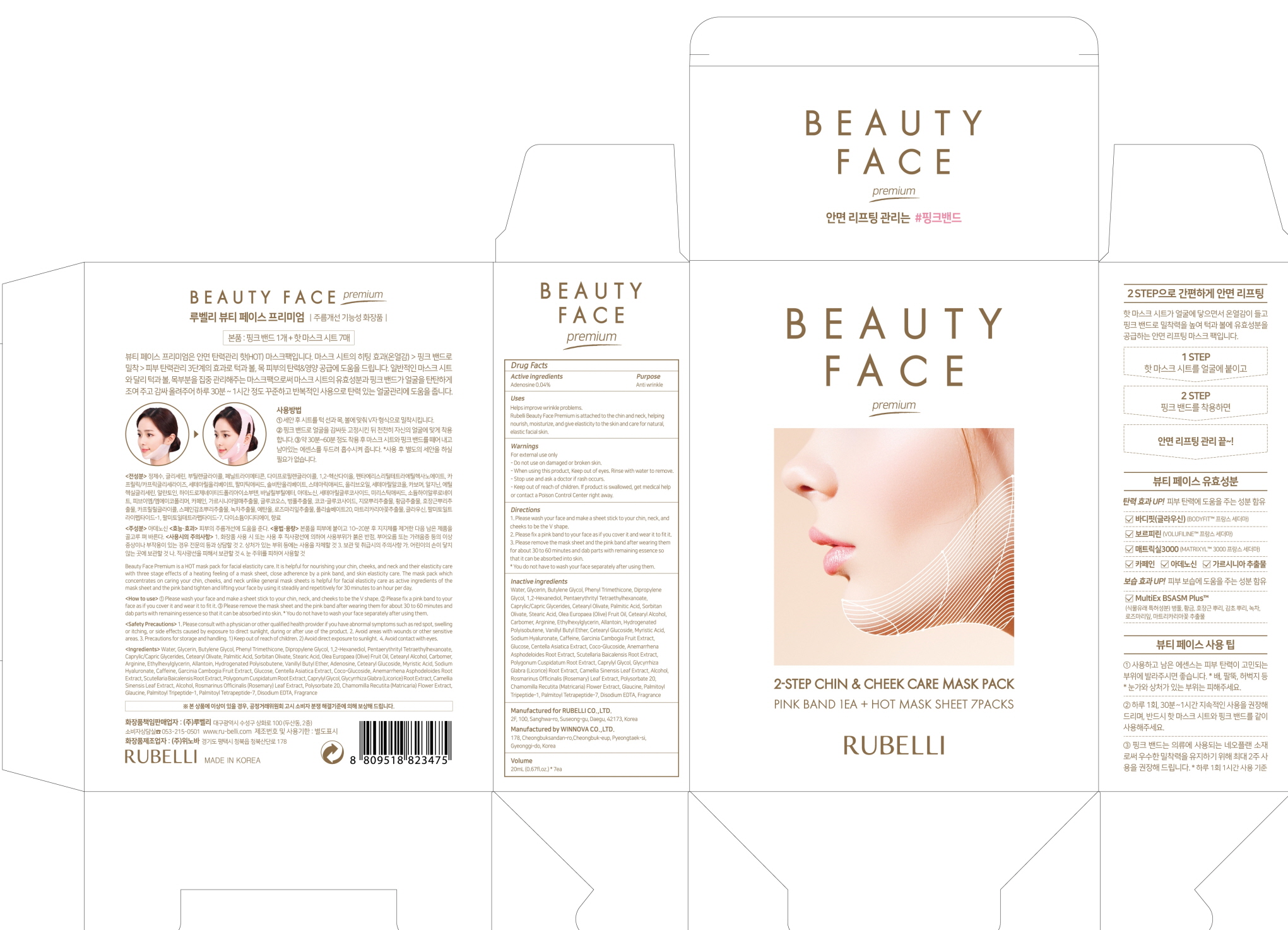 DRUG LABEL: RUBELLI BEAUTY FACE PREMIUM
NDC: 71006-090 | Form: PATCH
Manufacturer: RUBELLI CO.,LTD
Category: otc | Type: HUMAN OTC DRUG LABEL
Date: 20190529

ACTIVE INGREDIENTS: Adenosine 0.008 g/20 mL
INACTIVE INGREDIENTS: Water; Glycerin

ACTIVE INGREDIENT

Active ingredient: Adenosine 0.04%

INACTIVE INGREDIENT

Inactive ingredients:

Water, Glycerin, Butylene Glycol, Phenyl Trimethicone, Dipropylene Glycol, 1,2-Hexanediol, Pentaerythrityl Tetraethylhexanoate, Caprylic/Capric Glycerides, Cetearyl Olivate, Palmitic Acid, Sorbitan Olivate, Stearic Acid, Olea Europaea (Olive) Fruit Oil, Cetearyl Alcohol, Carbomer, Arginine, Ethylhexylglycerin, Allantoin, Hydrogenated Polyisobutene, Vanillyl Butyl Ether, Cetearyl Glucoside, Myristic Acid, Sodium Hyaluronate, Caffeine, Garcinia Cambogia Fruit Extract, Glucose, Centella Asiatica Extract, Coco-Glucoside, Anemarrhena Asphodeloides Root Extract, Scutellaria Baicalensis Root Extract, Polygonum Cuspidatum Root Extract, Caprylyl Glycol, Glycyrrhiza Glabra (Licorice) Root Extract, Camellia Sinensis Leaf Extract, Alcohol, Rosmarinus Officinalis (Rosemary) Leaf Extract, Polysorbate 20, Chamomilla Recutita (Matricaria) Flower Extract, Glaucine, Palmitoyl Tripeptide-1, Palmitoyl Tetrapeptide-7, Disodium EDTA, Fragrance

PURPOSE

Purpose: Anti wrinkle

WARNINGS

For external use only
- Do not use on damaged or broken skin
- When using this product, Keep out of eyes. Rinse with water to remove.
- Stop use and ask a doctor if rash occurs.
- Keep out of reach of children. If product is swallowed, get medical help or contact a Poison Control Center right away.

KEEP OUT OF REACH OF CHILDREN

Uses

Helps improve wrinkle problems.
Rubelli Beauty Face Premium is attached to the chin and neck, helping nourish, moisturize, and give elasticity to the skin and care for natural, elastic facial skin.

Directions

1. Please wash your face and make a sheet stick to your chin, neck, and cheeks to be the V shape.
2. Please fix a pink band to your face as if you cover it and wear it to fit it.
3. Please remove the mask sheet and the pink band after wearing them for about 30 to 60 minutes and dab parts with remaining essence so that it can be absorbed into skin.
* You do not have to wash your face separately after using them.